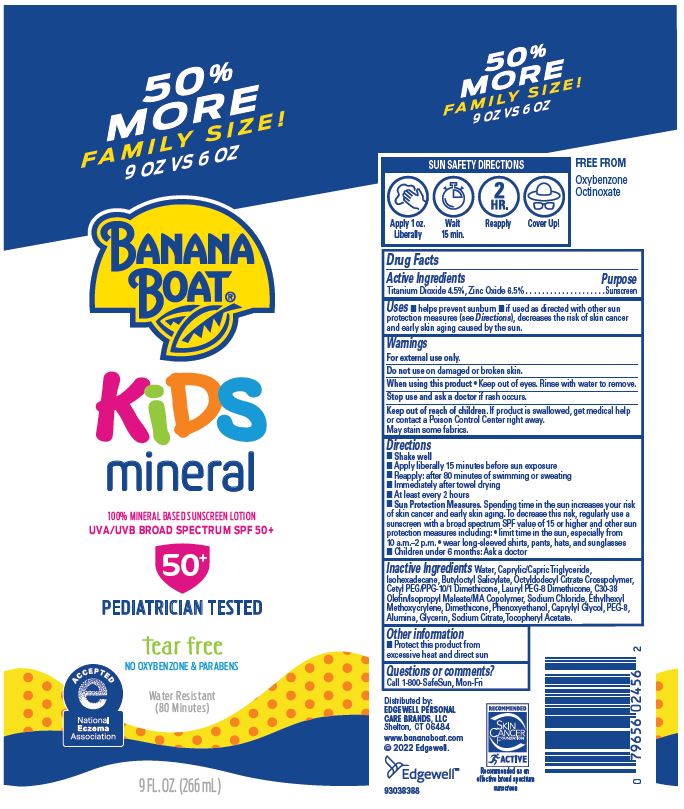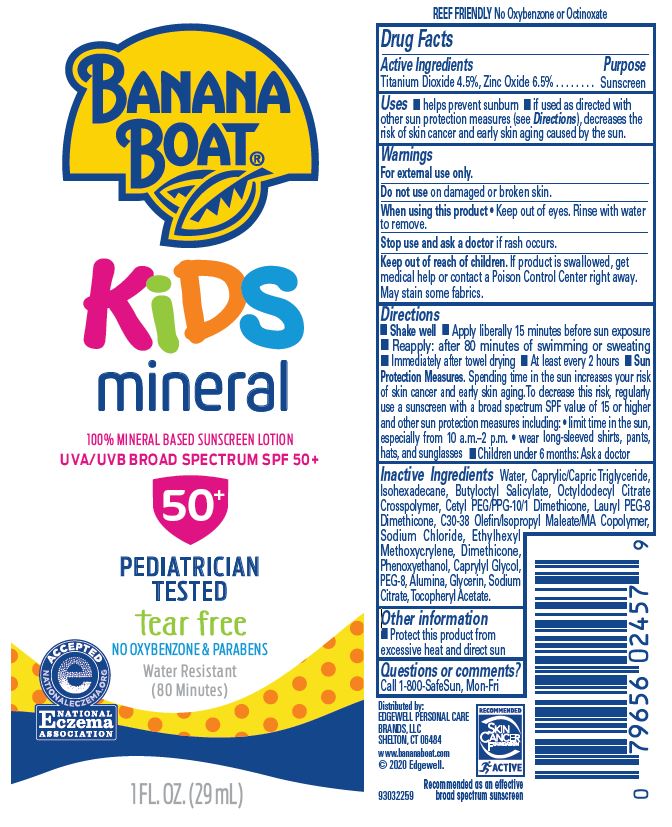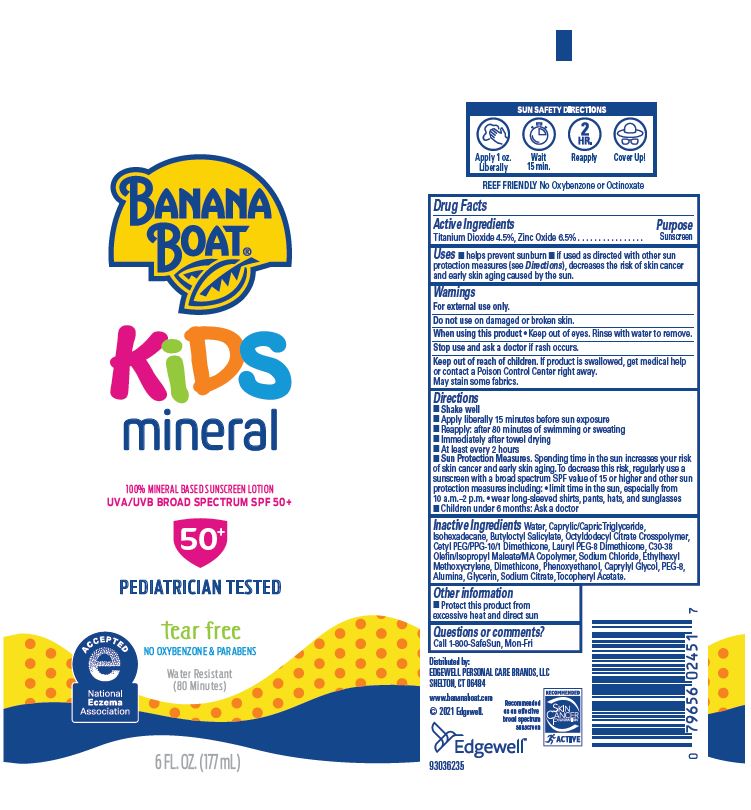 DRUG LABEL: Banana Boat Kids Mineral Protection SPF50
NDC: 63354-640 | Form: LOTION
Manufacturer: Edgewell Personal Care Brands LLC
Category: otc | Type: HUMAN OTC DRUG LABEL
Date: 20241027

ACTIVE INGREDIENTS: TITANIUM DIOXIDE 4.5 g/100 g; ZINC OXIDE 6.5 g/100 g
INACTIVE INGREDIENTS: MEDIUM-CHAIN TRIGLYCERIDES; SODIUM CHLORIDE; ALPHA-TOCOPHEROL ACETATE; BUTYLOCTYL SALICYLATE; WATER; ISOHEXADECANE; CETYL PEG/PPG-10/1 DIMETHICONE (HLB 2); ALUMINUM OXIDE; ETHYLHEXYL METHOXYCRYLENE; CAPRYLYL GLYCOL; GLYCERIN; ANHYDROUS TRISODIUM CITRATE; DIMETHICONE; PHENOXYETHANOL

Active Ingredients

Titanium Dioxide 4.5%, Zinc Oxide 6.5% .

Purpose

Sunscreen

Uses

- helps prevent sunburn
- if used as directed with other sun protection measures (see Directions), decreases the risk of skin cancer and early skin aging caused by the sun.

Warnings

For external use only.

May stain some fabrics.

Do not use

on damaged or broken skin.

When using this product

• Keep out of eyes. Rinse with water to remove

Stop use and ask a doctor

if rash occurs.

Keep out of reach of children.

If product is swallowed, get medical help or contact a Poison Control Center right away

Directions

• Shake well • Apply liberally 15 minutes before sun exposure • Reapply: after 80 minutes of swimming or sweating • Immediately after towel drying • At least every 2 hours • Sun Protection Measures. Spending time in the sun increases your risk of skin cancer and early skin aging. To decrease this risk, regularly use a sunscreen with a broad spectrum SPF value of 15 or higher and other sun protection measures including: • limit time in the sun, especially from 10 a.m.–2 p.m. • wear long-sleeved shirts, pants, hats, and sunglasses • Children under 6 months: Ask a doctor

Inactive Ingredients

Water, Caprylic/Capric Triglyceride, Isohexadecane, Butyloctyl Salicylate, Octyldodecyl Citrate Crosspolymer, Cetyl PEG/PPG-10/1 Dimethicone, Lauryl PEG-8 Dimethicone, C30-38 Olefin/Isopropyl Maleate/MA Copolymer, Sodium Chloride, Ethylhexyl Methoxycrylene, Dimethicone, Phenoxyethanol, Caprylyl Glycol, PEG-8, Alumina, Glycerin, Sodium Citrate, Tocopheryl Acetate.

Other information

Protect this product from excessive heat and direct sun

Questions or comments?

Call 1-800-SafeSun, Mon-Fri

PRINCIPAL DISPLAY PANEL

BANANA
BOAT®
KIDS
mineral
100% MINERAL BASED SUNSCREEN LOTION
UVA/UVB BROAD SPECTRUM SPF 50+
50+
PEDIATRICIAN TESTED
tear free
NO OXYBENZONE & PARABENS
Water Resistant
(80 Minutes)
1 FL.OZ.(29 mL)

BANANA
BOAT®
KIDS
mineral
100% MINERAL BASED SUNSCREEN LOTION
UVA/UVB BROAD SPECTRUM SPF 50+
50+
PEDIATRICIAN TESTED
tear free
NO OXYBENZONE & PARABENS
Water Resistant
(80 Minutes)
6 FL.OZ.(177 mL)

50%
MORE
FAMILY SIZE !
9 OZ VS 6 0Z
BANANA
BOAT®
KIDS
mineral
100% MINERAL BASED SUNSCREEN LOTION
UVA/UVB BROAD SPECTRUM SPF 50+
50+
PEDIATRICIAN TESTED
tear free
NO OXYBENZONE & PARABENS
Water Resistant
(80 Minutes)
9 FL.OZ.(266 mL)